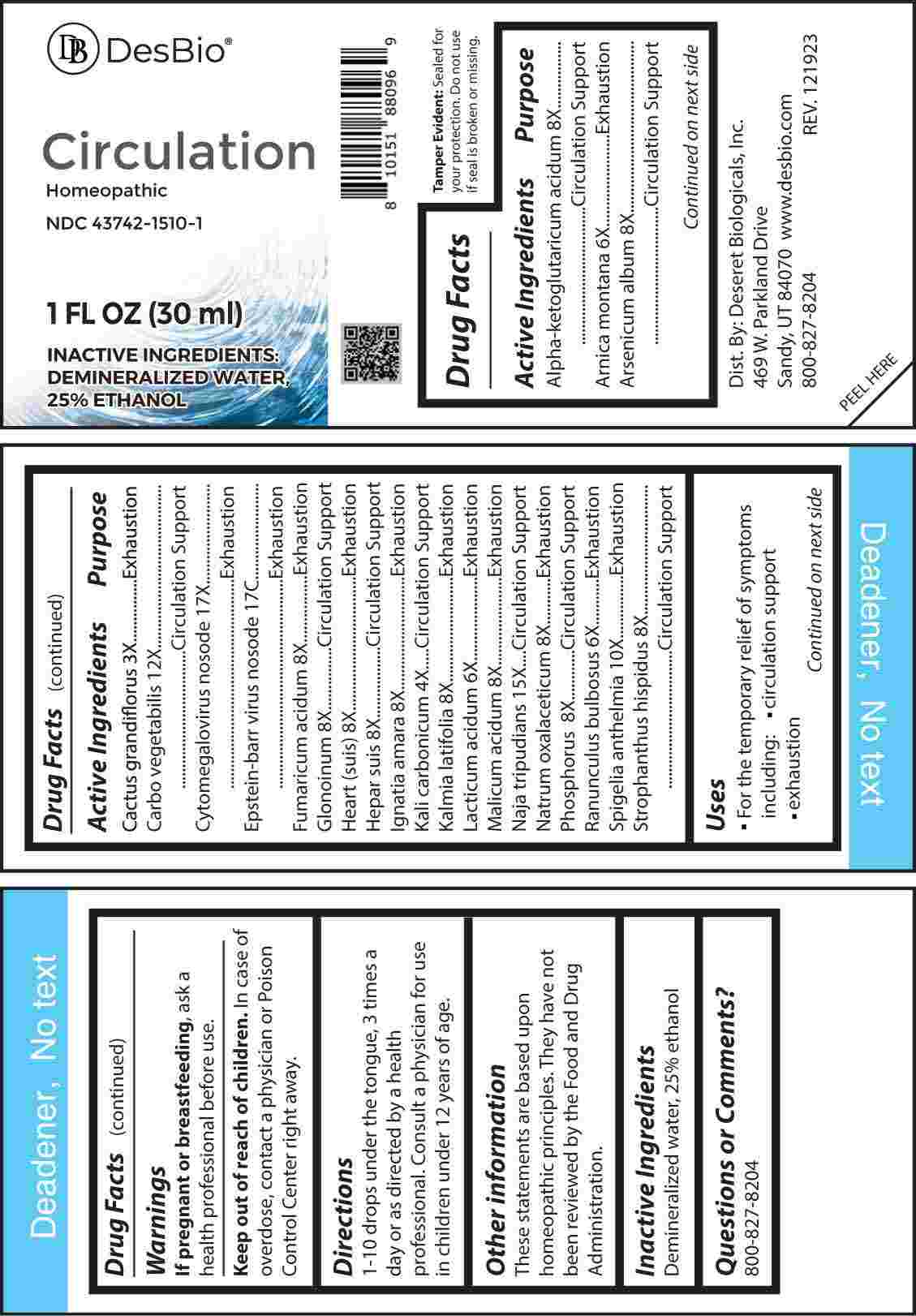 DRUG LABEL: Circulation
NDC: 43742-1510 | Form: LIQUID
Manufacturer: Deseret Biologicals, Inc.
Category: homeopathic | Type: HUMAN OTC DRUG LABEL
Date: 20240418

ACTIVE INGREDIENTS: SELENICEREUS GRANDIFLORUS STEM 3 [hp_X]/1 mL; POTASSIUM CARBONATE 4 [hp_X]/1 mL; ARNICA MONTANA WHOLE 6 [hp_X]/1 mL; LACTIC ACID 6 [hp_X]/1 mL; RANUNCULUS BULBOSUS WHOLE 6 [hp_X]/1 mL; OXOGLURIC ACID 8 [hp_X]/1 mL; ARSENIC TRIOXIDE 8 [hp_X]/1 mL; FUMARIC ACID 8 [hp_X]/1 mL; NITROGLYCERIN 8 [hp_X]/1 mL; PORK HEART 8 [hp_X]/1 mL; PORK LIVER 8 [hp_X]/1 mL; STRYCHNOS IGNATII SEED 8 [hp_X]/1 mL; KALMIA LATIFOLIA LEAF 8 [hp_X]/1 mL; MALIC ACID 8 [hp_X]/1 mL; SODIUM DIETHYL OXALACETATE 8 [hp_X]/1 mL; PHOSPHORUS 8 [hp_X]/1 mL; STROPHANTHUS HISPIDUS SEED 8 [hp_X]/1 mL; SPIGELIA ANTHELMIA WHOLE 10 [hp_X]/1 mL; ACTIVATED CHARCOAL 12 [hp_X]/1 mL; NAJA NAJA VENOM 15 [hp_X]/1 mL; HUMAN HERPESVIRUS 5 17 [hp_X]/1 mL; HUMAN HERPESVIRUS 4 17 [hp_C]/1 mL
INACTIVE INGREDIENTS: WATER; ALCOHOL

DRUG FACTS:

ACTIVE INGREDIENTS:

Alpha-Ketoglutaricum Acidum 8X, Arnica Montana 6X, Arsenicum Album 8X, Cactus Grandiflorus 3X, Carbo Vegetabilis 12X, Cytomegalovirus Nosode 17X, Epstein-Barr Virus Nosode 17C, Fumaricum Acidum 8X, Glonoinum 8X, Heart (Suis) 8X, Hepar Suis 8X, Ignatia Amara 8X, Kali Carbonicum 4X, Kalmia Latifolia 8X, Lacticum Acidum 6X, Malicum Acidum 8X, Naja Tripudians 15X, Natrum Oxalaceticum 8X, Phosphorus 8X, Ranunculus Bulbosus 6X, Spigelia Anthelmia 10X, Strophanthus Hispidus 8X.

PURPOSE:

Alpha-Ketoglutaricum Acidum – Circulation Support, Arnica Montana - Exhaustion, Arsenicum Album – Circulation Support, Cactus Grandiflorus - Exhaustion, Carbo Vegetabilis – Circulation Support, Cytomegalovirus Nosode - Exhaustion, Epstein-Barr Virus Nosode - Exhaustion, Fumaricum Acidum - Exhaustion, Glonoinum – Circulation Support, Heart (Suis) - Exhaustion , Hepar Suis – Circulation Support, Ignatia Amara - Exhaustion, Kali Carbonicum – Circulation Support, Kalmia Latifolia - Exhaustion, Lacticum Acidum - Exhaustion, Malicum Acidum - Exhaustion, Naja Tripudians – Circulation Support, Natrum Oxalaceticum - Exhaustion, Phosphorus – Circulation Support, Ranunculus Bulbosus - Exhaustion, Spigelia Anthelmia - Exhaustion, Strophanthus Hispidus – Circulation Support

USES:

• For the temporary relief of symptoms including:

• circulation support • exhaustion
These statements are based upon homeopathic principles. They have not been reviewed by the Food and Drug Administration.

WARNINGS:

If pregnant or breast-feeding, ask a health professional before use.

Keep out of reach of children. In case of overdose, contact a physician or Poison Control Center right away.
Tamper Evident: Sealed for your protection. Do not use if seal is broken or missing.

KEEP OUT OF REACH OF CHILDREN:

In case of overdose, contact a physician or Poison Control Center right away.

DIRECTIONS:

1-10 drops under the tongue, 3 times a day or as directed by a health professional. Consult a physician for use in children under 12 years of age.

INACTIVE INGREDIENTS:

Demineralized water, 25% ethanol

QUESTIONS:

Dist. By: Deseret Biologicals, Inc.
469 W. Parkland Drive
Sandy, UT 84070 www.desbio.com

PACKAGE LABEL DISPLAY:

Des Bio

Circulation

Homeopathic
NDC 43742-1510-1
1 FL OZ (30 ml)